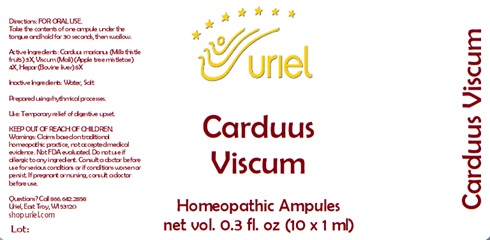 DRUG LABEL: Carduus Viscum
NDC: 48951-3032 | Form: LIQUID
Manufacturer: Uriel Pharmacy Inc.
Category: homeopathic | Type: HUMAN OTC DRUG LABEL
Date: 20241205

ACTIVE INGREDIENTS: MILK THISTLE 3 [hp_X]/1 mL; VISCUM ALBUM FRUITING TOP 4 [hp_X]/1 mL; MAMMAL LIVER 8 [hp_X]/1 mL
INACTIVE INGREDIENTS: WATER; SODIUM CHLORIDE

Carduus Viscum

INDICATIONS AND USAGE

Directions: FOR ORAL USE ONLY.

DOSAGE AND ADMINISTRATION

Take the contents of one ampule
under the tongue and hold for
30 seconds, then swallow.

ACTIVE INGREDIENT

Active Ingredients: Carduus marianus (Milk thistle fruits) 3X, Viscum Mali (Apple tree mistletoe) 4X,
Hepar (Bovine liver) 8X

Inactive Ingredients: Water, Salt

Prepared using rhythmical processes.

PURPOSE

Use: Temporary relief of digestive upset.

KEEP OUT OF REACH OF CHILDREN.

WARNINGS

Warnings: Claims based on traditional homeopathic practice, not accepted medical evidence. Not FDA evaluated. Do not use if allergic to any ingredient. Consult a doctor before use for serious conditions or if conditions worsen or persist. If pregnant or nursing, consult a doctor before use.

Questions? Call 866.642.2858
Uriel, East Troy, WI 53120
shopuriel.com Lot: